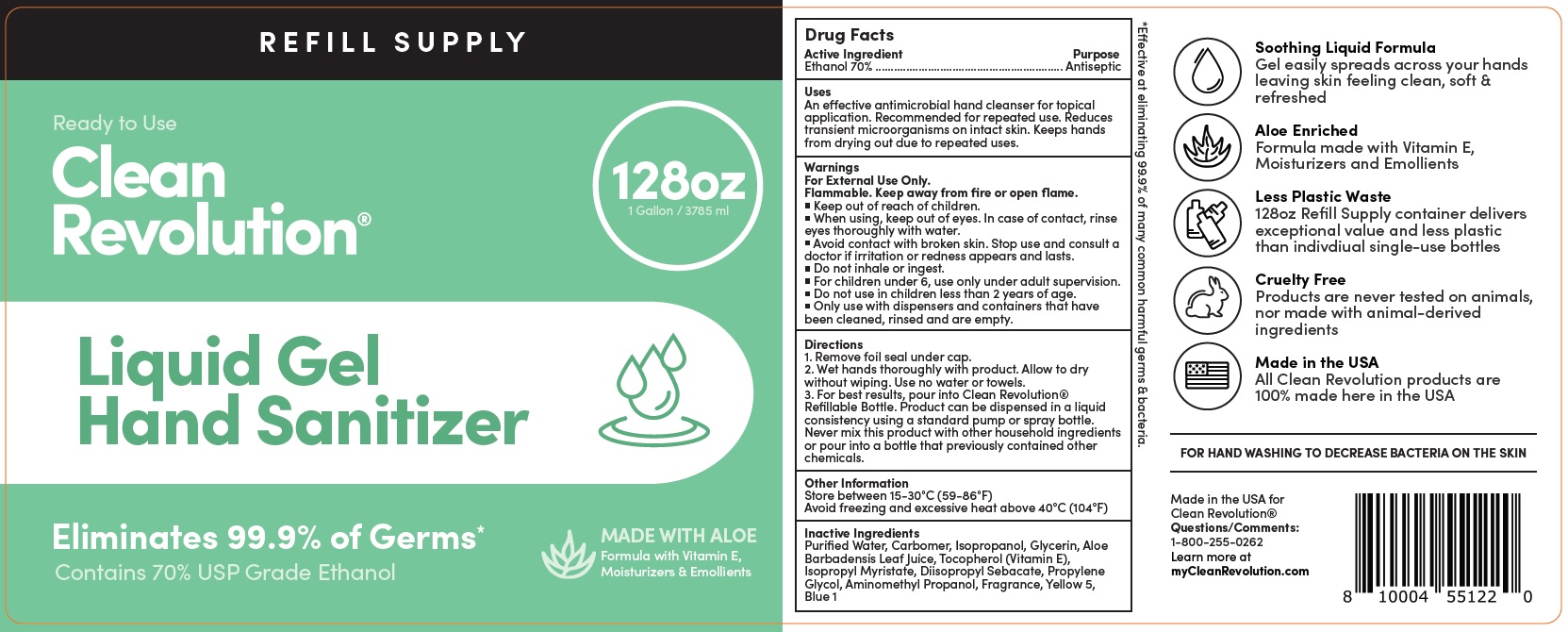 DRUG LABEL: Clean Revolution Hand Sanitizer Refill Supply Container - Gentle and Aloe Enriched - ELIMINATES 99.9% Germs - 70% Ethanol - Ready To Use
NDC: 74810-726 | Form: LIQUID
Manufacturer: Replenish Bottling LLC
Category: otc | Type: HUMAN OTC DRUG LABEL
Date: 20231226

ACTIVE INGREDIENTS: ALCOHOL 70 mL/100 mL
INACTIVE INGREDIENTS: WATER; CARBOMER HOMOPOLYMER, UNSPECIFIED TYPE; ISOPROPYL ALCOHOL; GLYCERIN; ALOE VERA LEAF; TOCOPHEROL; ISOPROPYL MYRISTATE; DIISOPROPYL SEBACATE; PROPYLENE GLYCOL; AMINOMETHYLPROPANOL; FD&C YELLOW NO. 5; FD&C BLUE NO. 1

Clean Revolution Liquid Gel Hand Sanitizer Refill Supply Container | Gentle & Aloe Enriched | ELIMINATES 99.9% Germs | 70% Ethanol | Ready To Use

Active Ingredient

Ethanol 70%

Purpose

Antiseptic

Uses

An effective antimicrobial hand cleanser for topical application. Recommended for repeated use. Reduces transient microorganisms on intact skin. Keeps hands from drying out due to repeated uses.

Warnings

For External Use Only.

Flammable. Keep away from fire or open flame.

When using,

- keep out of eyes. In case of contact, rinse eyes thoroughly with water.
- Avoid contact with borken skin.

Stop use and consult a doctor

- if irritation or redness appears and lasts.
- Do not inhale or ingest.
- For children under 6, use only under adult supervision.

Do not use

- in children less than 2 years of age.
- Only use with dispensers and containers that have been cleaned, rinsed and are empty.

Directions

1. Remove foil seal under cap.
2. Wet hands thoroughly with product. Allow to dry without wiping. Use no water or towels.
3. For best results, pour into Clean Revolution® Refillable Bottle. Product can be dispensed in a liquid consistency using a standard pump or spray bottle. Never mix this product with other household ingredients or pour into a bottle that previously contained other chemicals.

Other Information

Store between 15-30°C (59-86°F)
Avoid freezing and excessive heat above 40°C (104°F)

Inactive Ingredients

Purified Water, Carbomer, Isopropanol, Glycerin, Aloe Barbadensis Leaf Juice, Tocopherol (Vitamin E), Isopropyl Myristate, Diisopropyl Sebacate, Propylene Glycol, Aminomethyl Propanol, Fragrance, Yellow 5, Blue 1